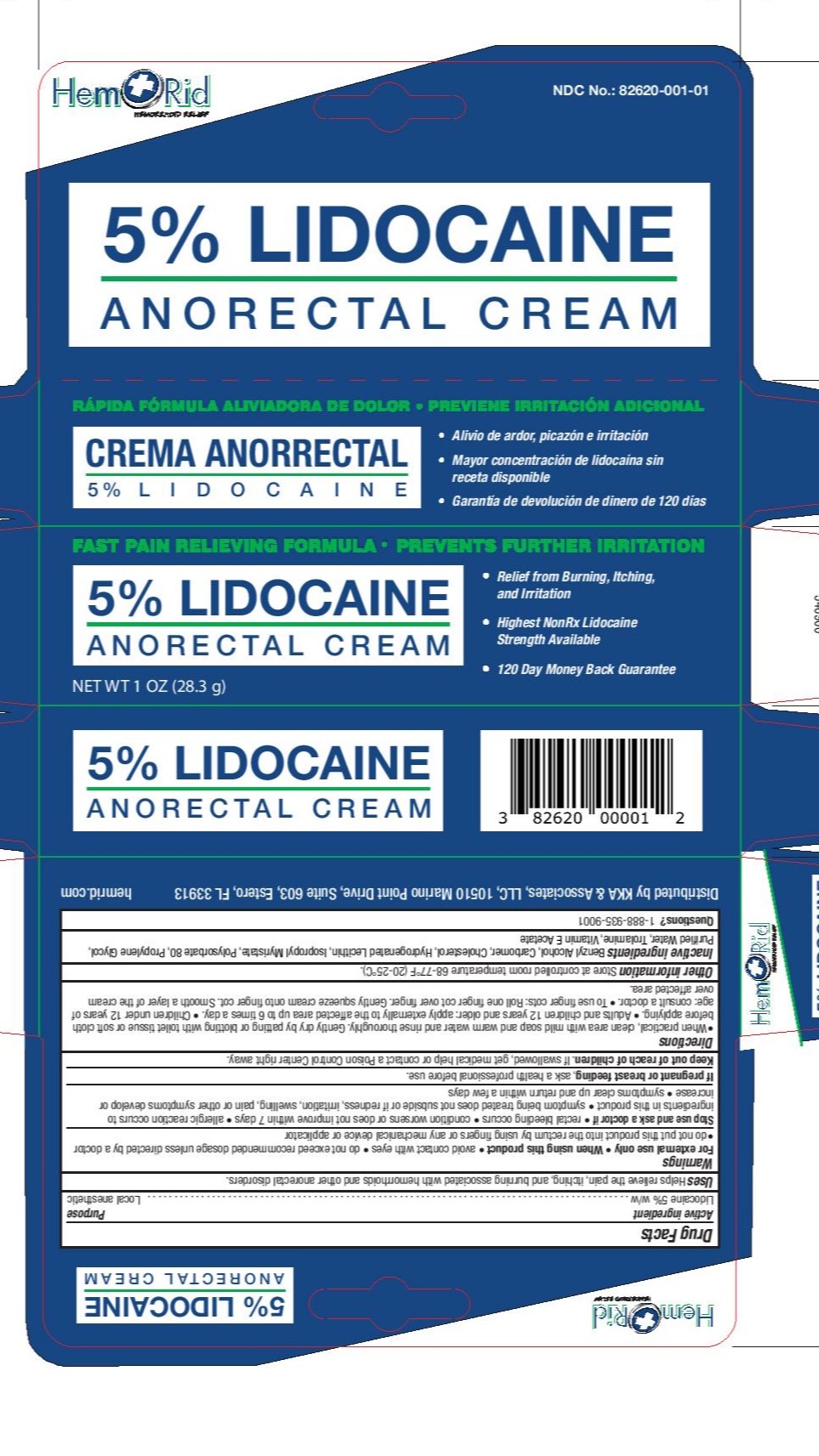 DRUG LABEL: HemRid Anorectal Cream
NDC: 82620-001 | Form: CREAM
Manufacturer: KKA & Associates LLC
Category: otc | Type: HUMAN OTC DRUG LABEL
Date: 20251231

ACTIVE INGREDIENTS: LIDOCAINE 50 mg/1 g
INACTIVE INGREDIENTS: TROLAMINE; .ALPHA.-TOCOPHEROL CALCIUM SUCCINATE, DL-; CHOLESTEROL; WATER; ISOPROPYL MYRISTATE; CARBOMER 940; BENZYL ALCOHOL; HYDROGENATED SOYBEAN LECITHIN; POLYSORBATE 80; PROPYLENE GLYCOL

Hemrid

INACTIVE INGREDIENT

Benzyl Alcohol, Carbomer, Cholesterol, Hydrogenated Lecithin (Soya), Isopropyl Myristate, Polysorbate 80, Propylene Glycol, Purified Water, Triethanolamine, Vitamin-E Acetate.

ACTIVE INGREDIENT

Lidocaine 5% W/W

PURPOSE

Local Anesthetic

DOSAGE AND ADMINISTRATION

When practical, cleanse the affected area with mild soap and warm water and rinse thoroughly, gently dry by patting or blotting with toilet tissue or a soft cloth before application of this product.
apply externally to the affected area up to 6 times a day.
Children under 12 years of age: consult a doctor.
To use with finger cot. Roll one finger cot over finger. Gently squeeze cream onto finger
Smooth a layer of the cream over the affected area.

Keep out of reach of children and pets. If swallowed, get medical help or contact a Poison Control Center right away.

WARNINGS

FOR EXTERNAL USE ONLY

When using this product

use only as directed.
Avoid contact with eyes.
do not exceed recommended dosage unless directed by a doctor.
do not out this product into the rectum by using fingers or any mechanical device or applicator.
Stop use and ask a doctor if
rectal bleeding occurs.
condition worsens or does not improve within 7 days.
symptoms clear up and occur again within a few days.
an allergic reaction develops to ingredients in this product.
symptom being treated does not subside or if redness, irritation, swelling, pain or other symptoms develop or increase.
If pregnant or breast-feeding, ask a health professional before use.

INDICATIONS AND USAGE

Helps relieve the pain, itching, and burning, associated with hemorrhoids and anorectal disorders.